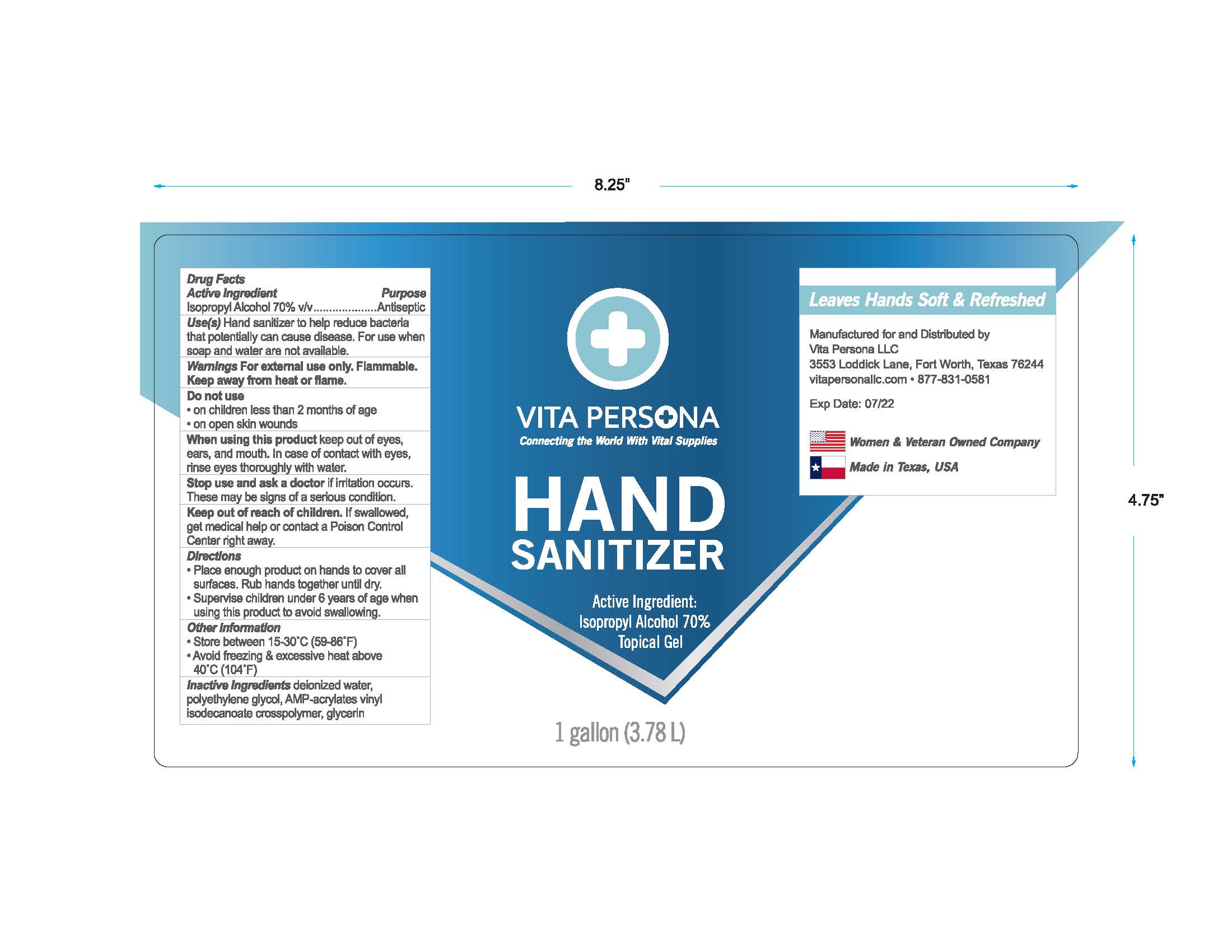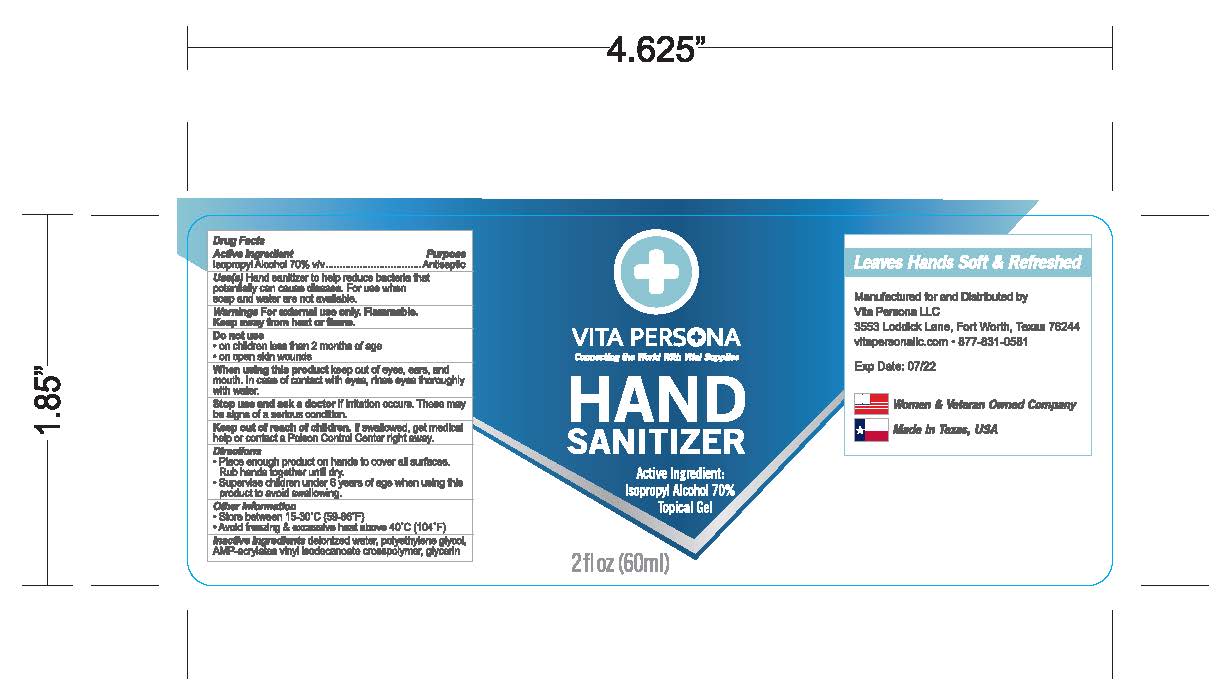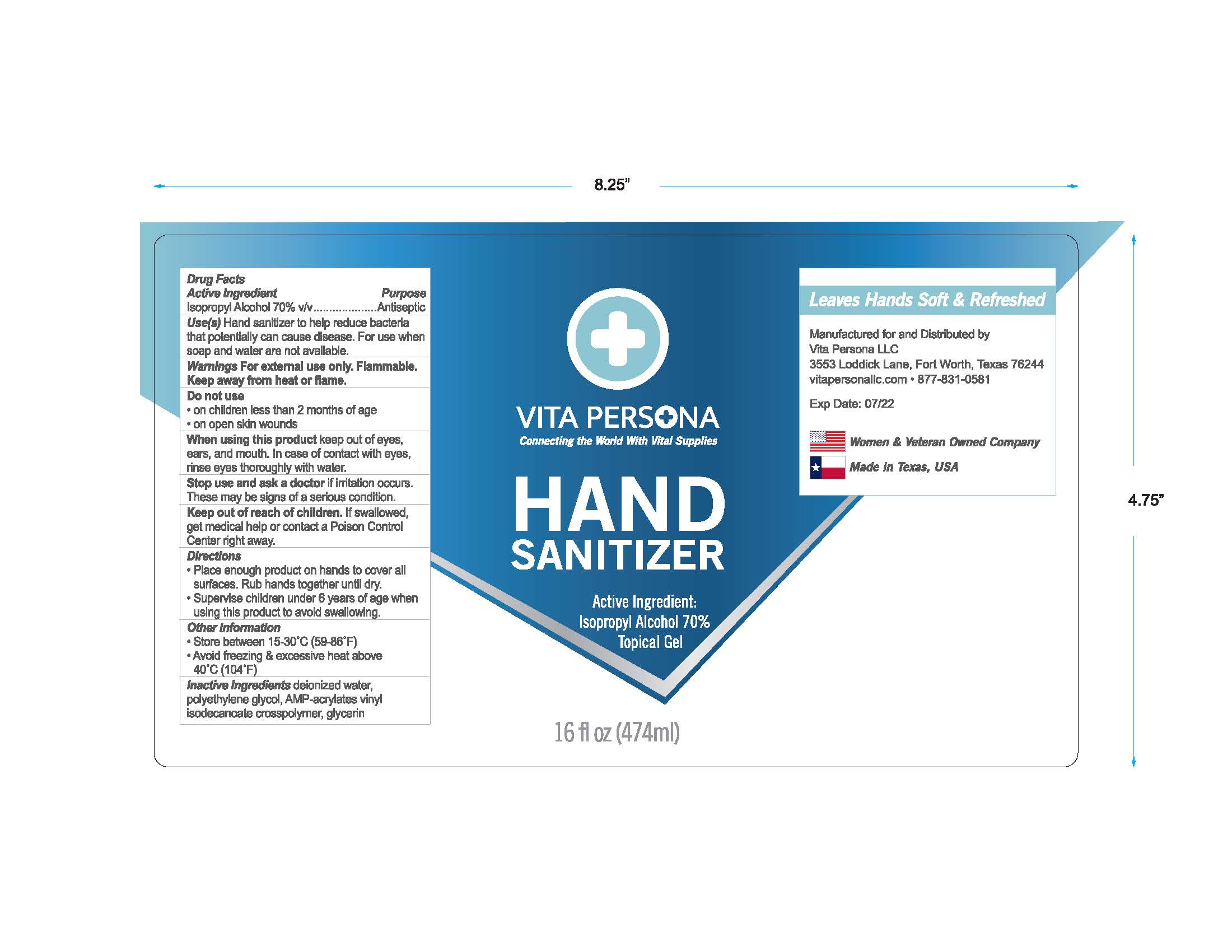 DRUG LABEL: Hand Sanitizer
NDC: 79839-360 | Form: GEL
Manufacturer: Enter Labeler Name
Category: otc | Type: HUMAN OTC DRUG LABEL
Date: 20200928

ACTIVE INGREDIENTS: ISOPROPYL ALCOHOL 70 mL/100 mL
INACTIVE INGREDIENTS: POLYETHYLENE GLYCOL, UNSPECIFIED; GLYCERIN; WATER; ACRYLATES/VINYL ISODECANOATE CROSSPOLYMER (10000 MPA.S NEUTRALIZED AT 0.5%)

The hand sanitizer is manufactured using only the following United States Pharmacopoeia (USP) grade ingredients in the preparation of the product (percentage in final product formulation) consistent with World Health Organization (WHO) recommendations:

1. Isopropyl Alcohol (70%) (ACTIB)
2. Water (IACT)
3. Polyethylene Glycol, Unspecified (IACT)
4. Aminomethylpropanol (IACT)
5. Acrylates/Vinyl Isodecanoate Crosspolymer (10000 MPA.S Neeutranlized at 0.5% (IACT)
6. Glycerin (IACT)

Active Ingredient(s)

Isopropyl Alcohol 70% v/v. Purpose: Antiseptic

Purpose

Antiseptic, Hand Sanitizer

Use

Hand Sanitizer to help reduce bacteria that potentially can cause disease. For use when soap and water are not available.

Warnings

For external use only. Flammable. Keep away from heat or flame

Do not use

- in children less than 2 months of age
- on open skin wounds

When using this product keep out of eyes, ears, and mouth. In case of contact with eyes, rinse eyes thoroughly with water.

Stop use and ask a doctor if irritation or rash occurs. These may be signs of a serious condition.

Keep out of reach of children. If swallowed, get medical help or contact a Poison Control Center right away.

Directions

- Place enough product on hands to cover all surfaces. Rub hands together until dry.
- Supervise children under 6 years of age when using this product to avoid swallowing.

Other information

- Store between 15-30C (59-86F)
- Avoid freezing and excessive heat above 40C (104F)

Inactive ingredients

deionized water, polyethylene glycol, AMP-acrylates vinyl isodecanoate crosspolymer, glycerin

Package Label - Principal Display Panel

60 ml NDC: 79839-360-02

474 ml NDC: 79839-360-16

3780 ml NDC: 79839-360-01